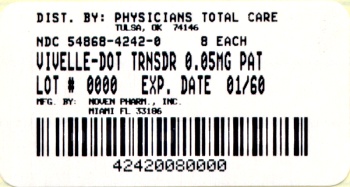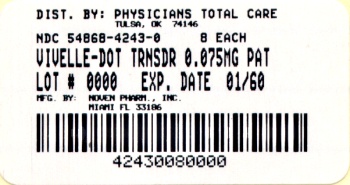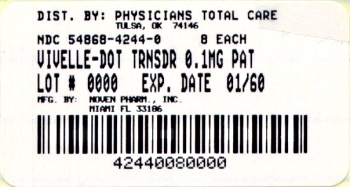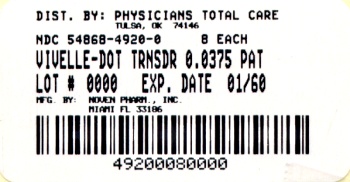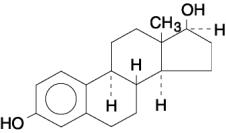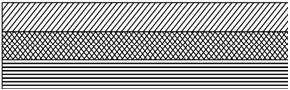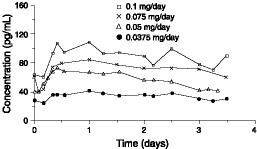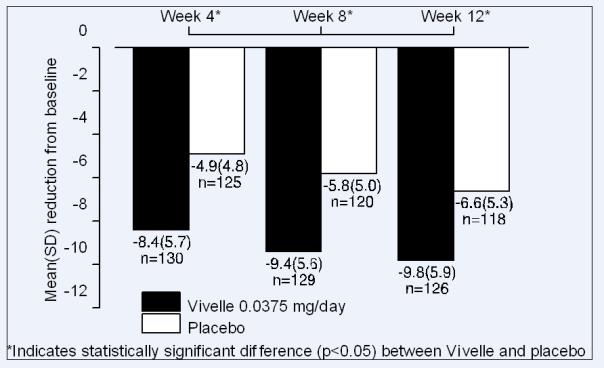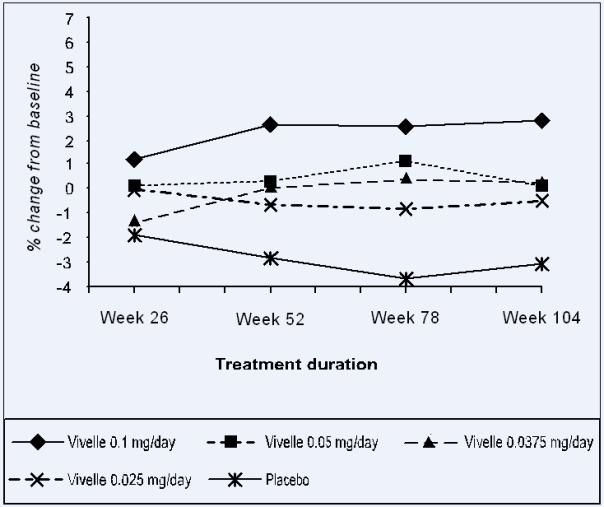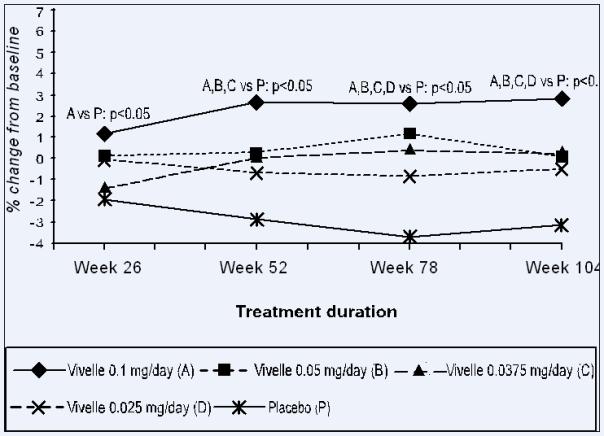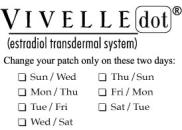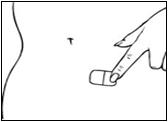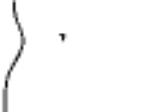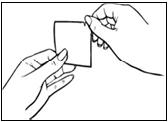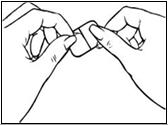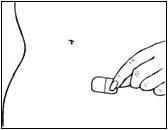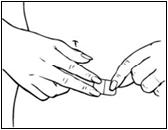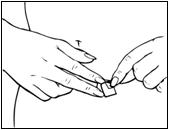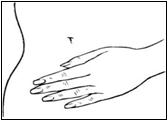 DRUG LABEL: Vivelle Dot
NDC: 54868-4862 | Form: PATCH, EXTENDED RELEASE
Manufacturer: Physicians Total Care, Inc.
Category: prescription | Type: HUMAN PRESCRIPTION DRUG LABEL
Date: 20120217

ACTIVE INGREDIENTS: ESTRADIOL 0.025 mg/1 d
INACTIVE INGREDIENTS: DIPROPYLENE GLYCOL; OLEYL ALCOHOL; POVIDONE

Vivelle-Dot

T2004-65/T2004-66

100922-6

Vivelle-Dot®

(estradiol transdermal system)

Continuous delivery for twice-weekly application

Rx only

Prescribing Information

BOXED WARNING

ESTROGENS INCREASE THE RISK OF ENDOMETRIAL CANCER

Close clinical surveillance of all women taking estrogens is important. Adequate diagnostic measures, including endometrial sampling when indicated, should be undertaken to rule out malignancy in all cases of undiagnosed persistent or recurring abnormal vaginal bleeding. There is no evidence that the use of “natural” estrogens results in a different endometrial risk profile than synthetic estrogens at equivalent estrogen doses. (See WARNINGS, Malignant Neoplasms, Endometrial Cancer.)

CARDIOVASCULAR AND OTHER RISKS

Estrogens with or without progestins should not be used for the prevention of cardiovascular disease. (See WARNINGS, Cardiovascular Disorders.)

The Women’s Health Initiative (WHI) study reported increased risks of myocardial infarction, stroke, invasive breast cancer, pulmonary emboli, and deep vein thrombosis in postmenopausal women (50 to 79 years of age), during 5 years of treatment with oral conjugated estrogens (CE 0.625 mg) combined with medroxyprogesterone acetate (MPA 2.5 mg) relative to placebo (see CLINICAL PHARMACOLOGY, Clinical Studies).

The Women’s Health Initiative Memory Study (WHIMS), a substudy of WHI, reported increased risk of developing probable dementia in postmenopausal women 65 years of age or older during 4 years of treatment with oral conjugated estrogens plus medroxyprogesterone acetate relative to placebo. It is unknown whether this finding applies to younger postmenopausal women or to women taking estrogen alone therapy. (See CLINICAL PHARMACOLOGY, Clinical Studies.)

Other doses of oral conjugated estrogens with medroxyprogesterone acetate, and other combinations and dosage forms of estrogens and progestins were not studied in the WHI clinical trials and, in the absence of comparable data, these risks should be assumed to be similar. Because of these risks, estrogens with or without progestins should be prescribed at the lowest effective doses and for the shortest duration consistent with treatment goals and risks for the individual woman.

DESCRIPTION

Vivelle-Dot® (estradiol transdermal system) contains estradiol in a multipolymeric adhesive. The system is designed to release estradiol continuously upon application to intact skin.

Five dosage strengths of Vivelle-Dot are available to provide nominal in vivo delivery rates of 0.025, 0.0375, 0.05, 0.075, or 0.1 mg of estradiol per day via the skin. Each corresponding system has an active surface area of 2.5, 3.75, 5.0, 7.5, or 10.0 cm^2 and contains 0.39, 0.585, 0.78, 1.17, or 1.56 mg of estradiol USP, respectively. The composition of the systems per unit area is identical.

Estradiol USP is a white, crystalline powder, chemically described as estra-1,3,5 (10)-triene-3,17β-diol.

The structural formula is

The molecular formula of estradiol is C18H2402. The molecular weight is 272.39.

Vivelle-Dot is comprised of three layers. Proceeding from the visible surface toward the surface attached to the skin, these layers are (1) a translucent polyolefin film (2) an adhesive formulation containing estradiol, acrylic adhesive, silicone adhesive, oleyl alcohol, NF, povidone, USP and dipropylene glycol, and (3) a polyester release liner which is attached to the adhesive surface and must be removed before the system can be used.

----- (1) Backing

----- (2) Adhesive Containing Estradiol

----- (3) Protective Liner

The active component of the system is estradiol. The remaining components of the system are pharmacologically inactive.

CLINICAL PHARMACOLOGY

Endogenous estrogens are largely responsible for the development and maintenance of the female reproductive system and secondary sexual characteristics. Although circulating estrogens exist in a dynamic equilibrium of metabolic interconversions, estradiol is the principal intracellular human estrogen and is substantially more potent than its metabolites, estrone and estriol, at the receptor level.

The primary source of estrogen in normally cycling adult women is the ovarian follicle, which secretes 70 to 500 mcg of estradiol daily, depending on the phase of the menstrual cycle. After menopause, most endogenous estrogen is produced by conversion of androstenedione, secreted by the adrenal cortex, to estrone by peripheral tissues. Thus, estrone and the sulfate conjugated form, estrone sulfate, are the most abundant circulating estrogens in postmenopausal women.

Estrogens act through binding to nuclear receptors in estrogen-responsive tissues. To date, two estrogen receptors have been identified. These vary in proportion from tissue to tissue.

Circulating estrogens modulate the pituitary secretion of the gonadotropins, luteinizing hormone (LH) and follicle stimulating hormone (FSH) through a negative feedback mechanism. Estrogens act to reduce the elevated levels of these hormones seen in postmenopausal women.

Pharmacokinetics

The skin metabolizes estradiol only to a small extent. In contrast, orally administered estradiol is rapidly metabolized by the liver to estrone and its conjugates, giving rise to higher circulating levels of estrone than estradiol. Therefore, transdermal administration produces therapeutic plasma levels of estradiol with lower circulating levels of estrone and estrone conjugates and requires smaller total doses than does oral therapy.

Absorption

In a multiple-dose study consisting of three consecutive system applications of the original formulation [Vivelle® (estradiol transdermal system)] which was conducted in 17 healthy, postmenopausal women, blood levels of estradiol and estrone were compared following application of these units to sites on the abdomen and buttocks in a crossover fashion. Systems that deliver nominal estradiol doses of approximately 0.0375 mg/day and 0.1 mg/day were applied to abdominal application sites while the 0.1 mg/day doses were also applied to sites on the buttocks. These systems increased estradiol levels above baseline within 4 hours and maintained respective mean levels of 25 and 79 pg/mL above baseline following application to the abdomen; slightly higher mean levels of 88 pg/mL above baseline were observed following application to the buttocks. At the same time, increases in estrone plasma concentrations averaged about 12 and 50 pg/mL, respectively, following application to the abdomen and 61 pg/mL for the buttocks. While plasma concentrations of estradiol and estrone remained slightly above baseline at 12 hours following removal of the systems in this study, results from another study show these levels to return to baseline values within 24 hours following removal of the systems.

Figure 1 illustrates the mean plasma concentrations of estradiol at steady-state during application of these patches at four different dosages.

Figure 1Steady-State Estradiol Plasma Concentrations for Systems Applied to the AbdomenNonbaseline-corrected levels

The corresponding pharmacokinetic parameters are summarized in the table below.

Table 1 Steady-State Estradiol Pharmacokinetic Parameters for Systems Applied to the Abdomen (mean ± standard deviation) Nonbaseline-corrected data*
Dosage (mg/day) | Cmax† (pg/mL) | Cavg‡ (pg/mL) | Cmin (84 hr)§ (pg/mL)
0.0375 | 46 ± 16 | 34 ± 10 | 30 ±10
0.05 | 83 ± 41 | 57 ± 23# | 41 ± 11#
0.075 | 99 ± 35 | 72 ± 24 | 60 ± 24
0.1 | 133 ± 51 | 89 ± 38 | 90 ± 44
0.1¶ | 145 ± 71 | 104 ± 52 | 85 ± 47

*Mean baseline estradiol concentration = 11.7 pg/mL

†Peak plasma concentration

‡Average plasma concentration

§Minimum plasma concentration at 84 hr

#Measured over 80 hr

¶Applied to the buttocks

Vivelle-Dot® (estradiol transdermal system), the revised formulation with smaller system sizes, was shown to be bioequivalent to the original formulation, Vivelle® (estradiol transdermal system), used in the clinical trials.

Distribution

No specific investigation of the tissue distribution of estradiol absorbed from Vivelle-Dot in humans has been conducted. The distribution of exogenous estrogens is similar to that of endogenous estrogens. Estrogens are widely distributed in the body and are generally found in higher concentrations in the sex hormone target organs. Estrogens circulate in the blood largely bound to sex hormone-binding globulin (SHBG) and albumin.

Metabolism

Exogenous estrogens are metabolized in the same manner as endogenous estrogens. Circulating estrogens exist in a dynamic equilibrium of metabolic interconversions. These transformations take place mainly in the liver. Estradiol is converted reversibly to estrone, and both can be converted to estriol, which is the major urinary metabolite. Estrogens also undergo enterohepatic recirculation via sulfate and glucuronide conjugation in the liver, biliary secretion of conjugates into the intestine, and hydrolysis in the gut followed by reabsorption. In postmenopausal women a significant portion of the circulating estrogens exist as sulfate conjugates, especially estrone sulfate, which serves as a circulating reservoir for the formation of more active estrogens.

Excretion

Estradiol, estrone and estriol are excreted in the urine along with glucuronide and sulfate conjugates. The half-life values calculated after dosing with the Vivelle-Dot ranged from 5.9 to 7.7 hours. After removal of the transdermal systems, serum concentrations of estradiol and estrone returned to baseline levels within 24 hours.

Special Populations

Vivelle-Dot was only investigated in postmenopausal women.

Drug Interactions

In vitro and in vivo studies have shown that estrogens are metabolized partially by cytochrome P450 3A4 (CYP3A4). Therefore, inducers or inhibitors of CYP3A4 may affect estrogen drug metabolism. Inducers of CYP3A4 such as St. John’s Wort preparations (Hypericum perforatum), phenobarbital, carbamazepine and rifampin may reduce plasma concentrations of estrogens, possibly resulting in a decrease in therapeutic effects and/or changes in the uterine bleeding profile. Inhibitors of CYP3A4 such as erythromycin, clarithromycin, ketoconazole, itraconazole, ritonavir and grapefruit juice may increase plasma concentrations of estrogens and may result in side effects.

Adhesion

Based on combined data from three short-term clinical trials consisting of 471 observations, 85% of Vivelle-Dot adhered completely to the skin over the 3.5-day wear period. Three (3%) of the systems detached and were reapplied or replaced during the 3.5-day wear period. Approximately 80% of the transdermal systems evaluated in these studies were Vivelle-Dot 0.05 mg/day.

Clinical Studies

Effects on vasomotor symptoms

In a pharmacokinetic study, Vivelle-Dot was shown to be bioequivalent to Vivelle. In two controlled clinical trials with Vivelle, of 356 subjects, the 0.075 and 0.1 mg doses were superior to placebo in relieving vasomotor symptoms at Week 4, and maintained efficacy through Weeks 8 and 12 of treatment. In this original study, the 0.0375 and 0.05 mg doses, however, did not differ from placebo until approximately Week 6, therefore, an additional 12-week placebo-controlled study in 255 patients was performed with Vivelle to establish the efficacy of the lowest dose of 0.0375 mg. The baseline mean daily number of hot flushes in these 255 patients was 11.5. Results at Weeks 4, 8, and 12 of treatment are shown in the figure below. (See Figure 2.)

Figure 2 Mean (SD) change from baseline in mean daily number of flushes for Vivelle® 0.0375 mg versus Placebo in a 12-week trial.

The 0.0375 mg dose was superior to placebo in reducing both the frequency and severity of vasomotor symptoms at Week 4 and maintained efficacy through Weeks 8 and 12 of treatment. All doses of Vivelle (0.0375 mg, 0.05 mg, 0.075 mg, and 0.1 mg) are effective for the control of vasomotor symptoms.

Effects on bone mineral density

Efficacy and safety of Vivelle in the prevention of postmenopausal osteoporosis have been studied in a 2-year double-blind, randomized, placebo-controlled, parallel group study. A total of 261 hysterectomized (161) and non-hysterectomized (100), surgically or naturally menopausal women (within 5 years of menopause), with no evidence of osteoporosis (lumbar spine bone mineral density within 2 standard deviations of average peak bone mass, i.e., ≥0.827 g/cm^2) were enrolled in this study; 194 patients were randomized to one of the four doses of Vivelle (0.1, 0.05, 0.0375, or 0.025 mg/day) and 67 patients to placebo. Over 2 years, study systems were applied to the buttock or the abdomen twice a week. Non-hysterectomized women received oral medroxyprogesterone acetate (2.5 mg/day) throughout the study.

The study population comprised naturally (82%) or surgically (18%) menopausal, hysterectomized (61%) or non-hysterectomized (39%) women with a mean age of 52.0 years (range 27 to 62 years); the mean duration of menopause was 31.7 months (range 2 to 72 months). Two hundred thirty-two (89%) of randomized subjects (173 on active drug, 59 on placebo) contributed data to the analysis of percent change from baseline in bone mineral density (BMD) of the AP lumbar spine, the primary efficacy variable. Patients were given supplemental dietary calcium (1000 mg elemental calcium/day) but no supplemental vitamin D. There was an increase in BMD of the AP lumbar spine in all Vivelle dose groups; in contrast to this, a decrease in AP lumbar spine BMD was observed in placebo patients. All Vivelle doses were significantly superior to placebo (p<0.05) at all time points with the exception of Vivelle 0.05 mg/day at 6 months. The highest dose of Vivelle was superior to the three lower doses. There were no statistically significant differences in pairwise comparisons among the three lower doses. (See Figure 3.)

Figure 3 Bone mineral density - AP Lumbar spine Least squares means of percentage change from baseline All randomized patients with at least one post-baseline assessment available with last post-baseline observation carried forward

Analysis of percent change from baseline in femoral neck BMD, a secondary efficacy outcome variable, showed qualitatively similar results; all doses of Vivelle were significantly superior to placebo (p<0.05) at 24 months. The highest Vivelle dose was superior to placebo at all time points. A mixture of significant and non-significant results were obtained for the lower dose groups at earlier time points. The highest Vivelle dose was superior to the three lower doses, and there were no significant differences among the three lower doses at this skeletal site. (See Figure 4.)

Figure 4 Bone mineral density - Femoral neck Least squares means of percentage change from baseline All randomized patients with at least one post-baseline assessment available with last post-baseline observation carried forward

The mean serum osteocalcin (a marker of bone formation) and urinary excretion of cross-link N-telopeptides of Type 1 collagen (a marker of bone resorption) decreased numerically in most of the active treatment groups relative to baseline. However, the decreases in both markers were inconsistent across treatment groups and the differences between active treatment groups and placebo were not statistically significant.

Women’s Health Initiative Studies

The Women’s Health Initiative (WHI) enrolled a total of 27,000 predominantly healthy postmenopausal women to assess the risks and benefits of the use of oral 0.625 mg conjugated estrogens (CE) per day alone or the use of oral 0.625 mg conjugated estrogens plus 2.5 mg medroxyprogesterone acetate (MPA) per day compared to placebo in the prevention of certain chronic diseases. The primary endpoint was the incidence of coronary heart disease (CHD) (non-fatal myocardial infarction and CHD death), with invasive breast cancer as the primary adverse outcome studied. A “global index” included the earliest occurrence of CHD, invasive breast cancer, stroke, pulmonary embolism (PE), endometrial cancer, colorectal cancer, hip fracture, or death due to other causes. The study did not evaluate the effects of CE or CE/MPA on menopausal symptoms.

The CE/MPA substudy was stopped early because, according to the predefined stopping rule, the increased risk of breast cancer and cardiovascular events exceeded the specified benefits included in the “global index”. Results of the CE/MPA substudy, which included 16,608 women (average age of 63 years, range 50 to 79, 83.9% White, 6.5% Black, 5.5% Hispanic), after an average follow-up of 5.2 years are presented in Table 2 below.

Table 2 Relative and Absolute Risk Seen in the CE/MPA Substudy of WHIa
EventC | RelativeRisk CE/MPAvs. Placebo at 5.2 Years (95% CI*) | Placebo n= 8102 Absolute Risk per 10,000 Women-Years | CE/MPA n= 8506
CHD events | 1.29 (1.02-1.63) | 30 | 37
Non-fatal MI | 1.32 (1.02-1.72) | 23 | 30
CHD death | 1.18 (0.70-1.97) | 6 | 7
Invasive breast cancerb | 1.26 (1.00-1.59) | 30 | 38
Stroke | 1.41 (1.07-1.85) | 21 | 29
Pulmonary embolism | 2.13 (1.39-3.25) | 8 | 16
Colorectal cancer | 0.63 (0.43-0.92) | 16 | 10
Endometrial cancer | 0.83 (0.47-1.47) | 6 | 5
Hip fracture | 0.66 (0.45-0.98) | 15 | 10
Death due to causes other than the events above | 0.92 (0.74-1.14) | 40 | 37
Global indexc | 1.15 (1.03-1.28) | 151 | 170
Deep vein thrombosisd | 2.07 (1.49-2.87) | 13 | 26
Vertebral fracturesd | 0.66 (0.44-0.98) | 15 | 9
Other osteoporotic fracturesd | 0.77 (0.69-0.86) | 170 | 131

a Adapted from JAMA, 2002: 288: 321-333

b Includes metastatic and non-metastatic breast cancer with the exception of in situ breast cancer

c A subset of the events was combined in a “global index”, defined as the earliest occurrence of CHD events, invasive breast cancer, stroke, pulmonary embolism, endometrial cancer, colorectal cancer, hip fracture, or death due to other causes

d Not included in Global index

* Nominal confidence intervals unadjusted for multiple looks and multiple comparisons

For those outcomes included in the “global index”, absolute excess risks per 10,000 women-years in the group treated with CE/MPA were 7 more CHD events, 8 more strokes, 8 more PEs, and 8 more invasive breast cancers, while absolute risk reductions per 10,000 women-years were 6 fewer colorectal cancers and 5 fewer hip fractures. The absolute excess risk of events included in the “global index” was 19 per 10,000 women-years. There was no difference between the groups in terms of all-cause mortality (See BOXED WARNINGS, WARNINGS, and PRECAUTIONS.)

Women’s Health Initiative Memory Study

The Women’s Health Initiative Memory Study (WHIMS), a substudy of WHI, enrolled 4,532 predominantly healthy postmenopausal women 65 years of age and older (47% were age 65 to 69 years, 35% were 70 to 74 years, and 18% were 75 years of age and older) to evaluate the effects of CE/MPA (0.625 mg conjugated estrogens plus 2.5 mg medroxyprogesterone acetate) on the incidence of probable dementia (primary outcome) compared with placebo.

After an average follow-up of 4 years, 40 women in the estrogen/progestin group (45 per 10,000 women-years) and 21 in the placebo group (22 per 10,000 women-years) were diagnosed with probable dementia. The relative risk of probable dementia in the hormone therapy group was 2.05 (95% CI, 1.21 to 3.48) compared to placebo. Differences between groups became apparent in the first year of treatment. It is unknown whether these findings apply to younger postmenopausal women. (See BOXED WARNINGS and WARNINGS, Dementia.)

INDICATIONS AND USAGE

Vivelle-Dot® (estradiol transdermal system) is indicated in:

1. Treatment of moderate to severe vasomotor symptoms associated with the menopause.
2. Treatment of moderate to severe symptoms of vulvar and vaginal atrophy associated with the menopause. When prescribing solely for the treatment of symptoms of vulvar and vaginal atrophy, topical vaginal products should be considered.
3. Treatment of hypoestrogenism due to hypogonadism, castration, or primary ovarian failure.
4. Prevention of postmenopausal osteoporosis. When prescribing solely for the prevention of postmenopausal osteoporosis, therapy should only be considered for women at significant risk of osteoporosis and non-estrogen medications should be carefully considered.

The mainstays for decreasing the risk of postmenopausal osteoporosis are weight-bearing exercise, adequate calcium and vitamin D intake, and when indicated, pharmacologic therapy. Postmenopausal women require an average of 1500 mg/day of elemental calcium. Therefore, when not contraindicated, calcium supplementation may be helpful for women with suboptimal dietary intake. Vitamin D supplementation of 400-800 IU/day may also be required to ensure adequate daily intake in postmenopausal women.

CONTRAINDICATIONS

Vivelle-Dot® (estradiol transdermal system) should not be used in women with any of the following conditions:

1. Undiagnosed abnormal genital bleeding.
2. Known, suspected or history of cancer of the breast.
3. Known or suspected estrogen-dependent neoplasia.
4. Active deep vein thrombosis, pulmonary embolism or a history of these conditions.
5. Active or recent (e.g., within the past year) arterial thromboembolic disease (e.g., stroke, myocardial infarction).
6. Liver dysfunction or disease.
7. Vivelle-Dotshould not be used in patients with known hypersensitivity to its ingredients.
8. Known or suspected pregnancy. There is no indication for Vivelle-Dot in pregnancy. There appears to be little or no increased risk of birth defects in children born to women who have used estrogens and progestins from oral contraceptives inadvertently during early pregnancy (see PRECAUTIONS).

WARNINGS

See BOXED WARNINGS.

The use of unopposed estrogens in women who have a uterus is associated with an increased risk of endometrial cancer.

1. Cardiovascular Disorders

Estrogen and estrogen/progestin therapy has been associated with an increased risk of cardiovascular events such as myocardial infarction and stroke, as well as venous thrombosis and pulmonary embolism (venous thromboembolism or VTE). Should any of these occur or be suspected, estrogens should be discontinued immediately.

Risk factors for arterial vascular disease (e.g., hypertension, diabetes mellitus, tobacco use, hypercholesterolemia, and obesity) and/or venous thromboembolism (e.g., personal history or family history of VTE, obesity, and systemic lupus erythematosus) should be managed appropriately.

a. Coronary Heart Disease and Stroke

In the Women’s Health Initiative (WHI) study, an increase in the number of myocardial infarctions and strokes has been observed in women receiving CE compared to placebo. These observations are preliminary. (See CLINICAL PHARMACOLOGY, Clinical Studies).

In the CE/MPA substudy of WHI an increased risk of coronary heart disease (CHD) events (defined as non-fatal myocardial infarction and CHD death) was observed in women receiving CE/MPA compared to women receiving placebo (37 vs 30 per 10,000 women-years). The increase in risk was observed in year one and persisted.

In the same substudy of WHI, an increased risk of stroke was observed in women receiving CE/MPA compared to women receiving placebo (29 vs 21 per 10,000 women-years). The increase in risk was observed after the first year and persisted.

In postmenopausal women with documented heart disease (n = 2,763, average age 66.7 years), a controlled clinical trial of secondary prevention of cardiovascular disease (Heart and Estrogen/Progestin Replacement Study; HERS) treatment with CE/MPA-0.625 mg/ 2.5 mg per day demonstrated no cardiovascular benefit. During an average follow-up of 4.1 years, treatment with CE/MPA did not reduce the overall rate of CHD events in postmenopausal women with established coronary heart disease. There were more CHD events in the CE/MPA-treated group than in the placebo group in year 1, but not during the subsequent years. Two thousand three hundred and twenty-one women from the original HERS trial agreed to participate in an open label extension of HERS, HERS II. Average follow-up in HERS II was an additional 2.7 years, for a total of 6.8 years overall. Rates of CHD events were comparable among women in the CE/MPA group and the placebo group in HERS, HERS II, and overall.

Large doses of estrogen (5 mg conjugated estrogens per day), comparable to those used to treat cancer of the prostate and breast, have been shown in a large prospective clinical trial in men to increase the risks of non-fatal myocardial infarction, pulmonary embolism, and thrombophlebitis.

b. Venous Thromboembolism (VTE)

In the Women’s Health Initiative (WHI) study, an increase in VTE has been observed in women receiving CE compared to placebo. These observations are preliminary (see CLINICAL PHARMACOLOGY, Clinical Studies).

In the CE/MPA substudy of WHI, a 2-fold greater rate of VTE, including deep venous thrombosis and pulmonary embolism, was observed in women receiving CE/MPA compared to women receiving placebo. The rate of VTE was 34 per 10,000 women-years in the CE/MPA group compared to 16 per 10,000 women-years in the placebo group. The increase in VTE risk was observed during the first year and persisted.

If feasible, estrogens should be discontinued at least 4 to 6 weeks before surgery of the type associated with an increased risk of thromboembolism, or during periods of prolonged immobilization.

2. Malignant Neoplasms

a. Endometrial Cancer

The use of unopposed estrogens in women with intact uteri has been associated with an increased risk of endometrial cancer. The reported endometrial cancer risk among unopposed estrogen users is about 2- to 12-fold greater than in non-users and appears dependent on duration of treatment and on estrogen dose. Most studies show no significant increased risk associated with the use of estrogens for less than 1 year. The greatest risk appears to be associated with prolonged use with increased risks of 15- to 24-fold for five to ten years or more, and this risk has been shown to persist for at least 8 to 15 years after estrogen therapy is discontinued.

Clinical surveillance of all women taking estrogen/progestin combinations is important. Adequate diagnostic measures, including endometrial sampling when indicated, should be undertaken to rule out malignancy in all cases of undiagnosed persistent or recurring abnormal vaginal bleeding. There is no evidence that the use of natural estrogens results in a different endometrial risk profile than synthetic estrogens of equivalent estrogen dose. Adding a progestin to estrogen therapy has been shown to reduce the risk of endometrial hyperplasia, which may be a precursor to endometrial cancer.

b. Breast Cancer

The use of estrogens and progestins by postmenopausal women has been reported to increase the risk of breast cancer. The most important randomized clinical trial providing information about this issue is the Women’s Health Initiative (WHI) substudy of CE/MPA (see CLINICAL PHARMACOLOGY, Clinical Studies). The results from observational studies are generally consistent with those of the WHI clinical trial and report no significant variation in the risk of breast cancer among different estrogens or progestins, doses, or routes of administration.

The CE/MPA substudy of WHI reported an increased risk of breast cancer in women who took CE/MPA for a mean follow-up of 5.6 years. Observational studies have also reported an increased risk for estrogen/progestin combination therapy, and a smaller increased risk for estrogen alone therapy, after several years of use. In the WHI trial and from observational studies, the excess risk increased with duration of use. From observational studies, the risk appeared to return to baseline in about five years after stopping treatment. In addition, observational studies suggest that the risk of breast cancer was greater, and became apparent earlier, with estrogen/progestin combination therapy as compared to estrogen alone therapy.

In the CE/MPA substudy, 26% of the women reported prior use of estrogen alone and/or estrogen/progestin combination hormone therapy. After a mean follow-up of 5.6 years during the clinical trial, the overall relative risk of invasive breast cancer was 1.24 (95% confidence interval 1.01-1.54), and the overall absolute risk was 41 vs 33 cases per 10,000 women-years, for CE/MPA compared with placebo. Among women who reported prior use of hormone therapy, the relative risk of invasive breast cancer was 1.86, and the absolute risk was 46 vs 25 cases per 10,000 women-years, for CE/MPA compared with placebo. Among women who reported no prior use of hormone therapy, the relative risk of invasive breast cancer was 1.09, and the absolute risk was 40 vs 36 cases per 10,000 women-years for CE/MPA compared with placebo. In the same substudy, invasive breast cancers were larger and diagnosed at a more advanced stage in the CE/MPA group compared with the placebo group. Metastatic disease was rare with no apparent difference between the two groups. Other prognostic factors such as histologic subtype, grade and hormone receptor status did not differ between the groups.

The use of estrogen plus progestin has been reported to result in an increase in abnormal mammograms requiring further evaluation. All women should receive yearly breast examinations by a healthcare provider and perform monthly breast self-examinations. In addition, mammography examinations should be scheduled based on patient age, risk factors, and prior mammogram results.

3. Dementia

In the Women’s Health Initiative Memory Study (WHIMS), 4,532 generally healthy postmenopausal women 65 years of age and older were studied, of whom 35% were 70 to 74 years of age and 18% were 75 or older. After an average follow-up of 4 years, 40 women being treated with CE/MPA (1.8%, n = 2,229) and 21 women in the placebo group (0.9%, n = 2,303) received diagnoses of probable dementia. The relative risk for CE/MPA vs placebo was 2.05 (95% confidence interval 1.21 – 3.48), and was similar for women with and without histories of menopausal hormone use before WHIMS. The absolute risk of probable dementia for CE/MPA vs placebo was 45 vs 22 cases per 10,000 women-years, and the absolute excess risk for CE/MPA was 23 cases per 10,000 women-years. It is unknown whether these findings apply to younger postmenopausal women. (See CLINICAL PHARMACOLOGY, Clinical Studies and PRECAUTIONS, Geriatric Use.) It is unknown whether these findings apply to estrogen alone therapy.

4. Gallbladder Disease

A 2- to 4-fold increase in the risk of gallbladder disease requiring surgery in postmenopausal women receiving estrogens has been reported.

5. Hypercalcemia

Administration of estrogen may lead to severe hypercalcemia in patients with breast cancer and bone metastases. If hypercalcemia occurs, use of the drug should be stopped and appropriate measures taken to reduce the serum calcium level.

6. Visual Abnormalities

Retinal vascular thrombosis has been reported in patients receiving estrogens. Discontinue medication pending examination if there is sudden partial or complete loss of vision, or a sudden onset of proptosis, diplopia, or migraine. If examination reveals papilledema or retinal vascular lesions, estrogens should be permanently discontinued.

PRECAUTIONS

A. General

1. Addition of a progestin when a woman has not had a hysterectomy. Studies of the addition of a progestin for 10 or more days of a cycle of estrogen administration, or daily with estrogen in a continuous regimen, have reported a lowered incidence of endometrial hyperplasia than would be induced by estrogen treatment alone. Endometrial hyperplasia may be a precursor to endometrial cancer. There are, however, possible risks that may be associated with the use of progestins with estrogens compared to estrogen-alone regimens. These include a possible increased risk of breast cancer.

2. Elevated Blood Pressure. In a small number of case reports, substantial increases in blood pressure have been attributed to idiosyncratic reactions to estrogens. In a large, randomized, placebo-controlled clinical trial, a generalized effect of estrogens on blood pressure was not seen. Blood pressure should be monitored at regular intervals with estrogen use.

3. Hypertriglyceridemia. In patients with pre-existing hypertriglyceridemia, estrogen therapy may be associated with elevations of plasma triglycerides leading to pancreatitis and other complications.

4. Impaired Liver Function and past history of cholestatic jaundice. Although transdermally administered estrogen therapy avoids first-pass hepatic metabolism, estrogens may be poorly metabolized in patients with impaired liver function. For patients with a history of cholestatic jaundice associated with past estrogen use or with pregnancy, caution should be exercised and in the case of recurrence, medication should be discontinued.

5. Hypothyroidism. Estrogen administration leads to increased thyroid-binding globulin (TBG) levels. Patients with normal thyroid function can compensate for the increased TBG by making more thyroid hormone, thus maintaining free T4 and T3 serum concentrations in the normal range. Patients dependent on thyroid hormone replacement therapy who are also receiving estrogens may require increased doses of their thyroid replacement therapy. These patients should have their thyroid function monitored in order to maintain their free thyroid hormone levels in an acceptable range.

6. Fluid Retention. Because estrogens may cause some degree of fluid retention, patients with conditions that might be influenced by this factor, such as cardiac or renal dysfunction, warrant careful observation when estrogens are prescribed.

7. Hypocalcemia. Estrogens should be used with caution in individuals with severe hypocalcemia.

8. Ovarian Cancer. The CE/MPA substudy of WHI reported that estrogen plus progestin increased the risk of ovarian cancer. After an average follow-up of 5.6 years, the relative risk for ovarian cancer for CE/MPA vs placebo was 1.58 (95% confidence interval 0.77 – 3.24) but was not statistically significant. The absolute risk for CE/MPA vs placebo was 4.2 vs 2.7 cases per 10,000 women-years. In some epidemiologic studies, the use of estrogen alone, in particular for ten or more years, has been associated with an increased risk of ovarian cancer. Other epidemiologic studies have not found these associations.

9. Exacerbation of Endometriosis. Endometriosis may be exacerbated with administration of estrogens. A few cases of malignant transformation of residual endometrial implants have been reported in women treated post-hysterectomy with estrogen alone therapy. For patients known to have residual endometriosis post-hysterectomy, the addition of progestin should be considered.

10. Exacerbation of Other Conditions. Estrogens may cause an exacerbation of asthma, diabetes mellitus, epilepsy, migraines or porphyria, systemic lupus erythematosus, and hepatic hemangiomas and should be used with caution in women with these conditions.

B. Patient Information.

Physicians are advised to discuss the Patient Information leaflet with patients for whom they prescribe Vivelle-Dot® (estradiol transdermal system).

C. Laboratory Tests.

Estrogen administration should be initiated at the lowest dose approved for the indication and then guided by clinical response, rather than by serum hormone levels (e.g., estradiol, FSH).

D. Drug/Laboratory Test Interactions.

1. Accelerated prothrombin time, partial thromboplastin time, and platelet aggregation time; increased platelet count; increased factors II, VII antigen, VIII antigen, VIII coagulant activity, IX, X, XII, VII-X complex, II-VII-X complex; and beta-thromboglobulin; decreased levels of anti-factor Xa and antithrombin III; decreased antithrombin III activity; increased levels of fibrinogen and fibrinogen activity; increased plasminogen antigen and activity.
2. Increased thyroid-binding globulin (TBG) leading to increased circulating total thyroid hormone levels, as measured by protein-bound iodine (PBI), T4 levels (by column or by radioimmunoassay) or T3 levels by radioimmunoassay. T3 resin uptake is decreased, reflecting the elevated TBG. Free T4 and free T3 concentrations are unaltered. Patients on thyroid replacement therapy may require higher doses of thyroid hormone.
3. Other binding proteins may be elevated in serum (i.e., corticosteroid-binding globulin [CBG], sex hormone-binding globulin [SHBG]), leading to increased total circulating corticosteroids and sex steroids, respectively. Free hormone concentrations may be decreased. Other plasma proteins may be increased (angiotensinogen/renin substrate, alpha-1-antitrypsin, ceruloplasmin).
4. Increased plasma HDL and HDL2 cholesterol subfraction concentrations, reduced LDL cholesterol concentration, increased triglycerides levels.
5. Impaired glucose tolerance.
6. Reduced response to metyrapone test.

E. Carcinogenesis, Mutagenesis, Impairment of Fertility.

Long-term, continuous administration of estrogen, with and without progestin, in women with and without a uterus, has shown an increased risk of endometrial cancer, breast cancer, and ovarian cancer. (See BOXED WARNINGS, WARNINGS, and PRECAUTIONS.)

Long-term, continuous administration of natural and synthetic estrogens in certain animal species increases the frequency of carcinomas of the breast, uterus, cervix, vagina, testis, and liver.

F. Pregnancy.

Vivelle-Dot should not be used during pregnancy. (See CONTRAINDICATIONS.)

G. Nursing Mothers.

Estrogen administration to nursing mothers has been shown to decrease the quantity and quality of the milk. Detectable amounts of estrogens have been identified in the milk of mothers receiving this drug. Caution should be exercised when Vivelle-Dot is administered to a nursing woman.

H. Pediatric Use.

Estrogen therapy has been used for the induction of puberty in adolescents with some forms of pubertal delay. Safety and effectiveness in pediatric patients have not otherwise been established.

Large and repeated doses of estrogen over an extended time period have been shown to accelerate epiphyseal closure, which could result in short adult stature if treatment is initiated before the completion of physiologic puberty in normally developing children. If estrogen is administered to patients whose bone growth is not complete, periodic monitoring of bone maturation and effects on epiphyseal centers is recommended during estrogen administration.

Estrogen treatment of prepubertal girls also induces premature breast development and vaginal cornification, and may induce vaginal bleeding. (See INDICATIONS and DOSAGE AND ADMINISTRATION.)

I. Geriatric Use.

The safety and effectiveness in geriatric patients have not been established.

In the Women’s Health Initiative Memory Study, including 4,532 women 65 years of age and older, followed for an average of 4 years, 82% (n = 3,729) were 65 to 74 while 18% (n = 803) were 75 and over. Most women (80%) had no prior hormone therapy use. Women treated with conjugated estrogens plus medroxyprogesterone acetate were reported to have a two-fold increase in the risk of developing probable dementia. Alzheimer’s disease was the most common classification of probable dementia in both the conjugated estrogens plus medroxyprogesterone acetate group and the placebo group. Ninety percent of the cases of probable dementia occurred in the 54% of women that were older than 70. (See WARNINGS, Dementia.) It is unknown whether these findings apply to estrogen alone therapy.

ADVERSE REACTIONS

See BOXED WARNINGS, WARNINGS and PRECAUTIONS.

Because clinical trials are conducted under widely varying conditions, adverse reaction rates observed in the clinical trials of a drug cannot be directly compared to rates in the clinical trials of another drug and may not reflect the rates observed in practice. The adverse reaction information from clinical trials does, however, provide a basis for identifying the adverse events that appear to be related to drug use and for approximating rates.

The following adverse events have been reported with Vivelle-Dot® (estradiol transdermal system) therapy:

Table 3 Summary of Most Frequently Reported Adverse Experiences/Medical Events Regardless of Relationship Reported at a Frequency ≥5%
 | Vivelle 0.025 mg/day† (N=47) N (%) | Vivelle 0.0375 mg/day† (N=130) N (%) | Vivelle 0.05 mg/day† (N=103) N (%) | Vivelle 0.075 mg/day† (N=46) N (%) | Vivelle 0.1 mg/day† (N=132) N (%) | Placebo (N=157) N (%)
Gastrointestinal disorders
Constipation | 2 (4.3) | 5 (3.8) | 4 (3.9) | 3 (6.5) | 2 (1.5) | 4 (2.5)
Dyspepsia | 4 (8.5) | 12 (9.2) | 3 (2.9) | 2 (4.3) | 0 | 10 (6.4)
Nausea | 2 (4.3) | 8 (6.2) | 4 (3.9) | 0 | 7 (5.3) | 5 (3.2)
General disorders and
administration site
conditions***
Influenza-like illness | 3 (6.4) | 6 (4.6) | 8 (7.8) | 0 | 3 (2.3) | 10 (6.4)
Pain NOS* | 0 | 8 (6.2) | 0 | 2 (4.3) | 7 (5.3) | 7 (4.5)
Infections and infestations
Influenza | 4 (8.5) | 4 (3.1) | 6 (5.8) | 0 | 10 (7.6) | 14 (8.9)
Nasopharyngitis | 3 (6.4) | 16 (12.3) | 10 (9.7) | 9 (19.6) | 11 (8.3) | 24 (15.3)
Sinusitis NOS* | 4 (8.5) | 17 (13.1) | 13 (12.6) | 3 (6.5) | 7 (5.3) | 16 (10.2)
Upper respiratory tract infection NOS* | 3 (6.4) | 8 (6.2) | 11 (10.7) | 4 (8.7) | 6 (4.5) | 9 (5.7)
Investigations
Weight increased | 4 (8.5) | 5 (3.8) | 2 (1.9) | 2 (4.3) | 0 | 3 (1.9)
Musculoskeletal and connective
tissue disorders
Arthralgia | 0 | 11 (8.5) | 4 (3.9) | 2 (4.3) | 5 (3.8) | 9 (5.7)
Back pain | 4 (8.5) | 10 (7.7) | 9 (8.7) | 4 (8.7) | 14 (10.6) | 10 (6.4)
Neck pain | 3 (6.4) | 4 (3.1) | 4 (3.9) | 0 | 6 (4.5) | 2 (1.3)
Pain in limb | 0 | 10 (7.7) | 7 (6.8) | 2 (4.3) | 6 (4.5) | 9 (5.7)
Nervous system disorders
Headache NOS* | 7 (14.9) | 35 (26.9) | 32 (31.1) | 23 (50.0) | 34 (25.8) | 37 (23.6)
Sinus headache | 0 | 12 (9.2) | 5 (4.9) | 5 (10.9) | 2 (1.5) | 8 (5.1)
Psychiatric disorders
Anxiety NEC** | 3 (6.4) | 5 (3.8) | 0 | 0 | 2 (1.5) | 4 (2.5)
Depression | 5 (10.6) | 4 (3.1) | 7 (6.8) | 0 | 4 (3.0) | 6 (3.8)
Insomnia | 3 (6.4) | 6 (4.6) | 4 (3.9) | 2 (4.3) | 2 (1.5) | 9 (5.7)
Reproductive system and
breast disorders
Breast tenderness | 8 (17.0) | 10 (7.7) | 8 (7.8) | 3 (6.5) | 17 (12.9) | 0
Dysmenorrhea | 0 | 0 | 0 | 3 (6.5) | 0 | 0
Intermenstrual bleeding | 3 (6.4) | 9 (6.9) | 6 (5.8) | 0 | 14 (10.6) | 7 (4.5)
Respiratory, thoracic and
mediastinal disorders
Sinus congestion | 0 | 4 (3.1) | 3 (2.9) | 3 (6.5) | 6 (4.5) | 7 (4.5)
Vascular disorders
Hot flushes NOS* | 3 (6.4) | 0 | 3 (2.9) | 0 | 0 | 6 (3.8)
Hypertension NOS* | 2 (4.3) | 0 | 3 (2.9) | 0 | 0 | 2 (1.3)

† Represents milligrams of estradiol delivered daily by each system

* NOS represents not otherwise specified

** NEC represents not elsewhere classified

*** Application site erythema and application site irritation were observed in a small number of patients (3.2% or less of patients across treatment groups.)

The following additional adverse reactions have been reported with estrogen and/or progestin therapy:

1. Genitourinary system. Changes in vaginal bleeding pattern and abnormal withdrawal bleeding or flow; breakthrough bleeding; spotting; dysmenorrhea, increase in size of uterine leiomyomata; vaginitis, including vaginal candidiasis; change in amount of cervical secretion; changes in cervical ectropion; ovarian cancer; endometrial hyperplasia; endometrial cancer.

2. Breasts. Tenderness, enlargement, pain, nipple discharge, galactorrhea; fibrocystic breast changes; breast cancer.

3. Cardiovascular. Deep and superficial venous thrombosis; pulmonary embolism; thrombophlebitis; myocardial infarction; stroke; increase in blood pressure.

4. Gastrointestinal. Nausea, vomiting; abdominal cramps, bloating; cholestatic jaundice; increased incidence of gallbladder disease; pancreatitis, enlargement of hepatic hemangiomas.

5. Skin. Chloasma or melasma, which may persist when drug is discontinued; erythema multiforme; erythema nodosum; hemorrhagic eruption; loss of scalp hair; hirsutism; pruritus, rash.

6. Eyes. Retinal vascular thrombosis; intolerance to contact lenses.

7. Central nervous system. Headache; migraine; dizziness; mental depression; chorea; nervousness; mood disturbances; irritability; exacerbation of epilepsy, dementia.

8. Miscellaneous. Increase or decrease in weight; reduced carbohydrate tolerance; aggravation of porphyria; edema; arthralgias; leg cramps; changes in libido; anaphylactoid/anaphylactic reactions including urticaria and angioedema; hypocalcemia; exacerbation of asthma; increased triglycerides.

OVERDOSAGE

Serious ill effects have not been reported following acute ingestion of large doses of estrogen-containing drug products by young children. Overdosage of estrogen may cause nausea and vomiting, and withdrawal bleeding may occur in females.

DOSAGE AND ADMINISTRATION

The adhesive side of Vivelle-Dot® (estradiol transdermal system) should be placed on a clean, dry area of the abdomen. Vivelle-Dot should not be applied to the breasts. Vivelle-Dot should be replaced twice weekly. The sites of application must be rotated, with an interval of at least 1 week allowed between applications to a particular site. The area selected should not be oily, damaged, or irritated. The waistline should be avoided, since tight clothing may rub the system off. The system should be applied immediately after opening the pouch and removing the protective liner. The system should be pressed firmly in place with the palm of the hand for about 10 seconds, making sure there is good contact, especially around the edges. In the event that a system should fall off, the same system may be reapplied. If the same system cannot be reapplied, a new system should be applied to another location. In either case, the original treatment schedule should be continued. If a woman has forgotten to apply a patch, she should apply a new patch as soon as possible. The new patch should be applied on the original treatment schedule. The interruption of treatment in women taking Vivelle-Dot might increase the likelihood of breakthrough bleeding, spotting and recurrence of symptoms.

Initiation of Therapy

When estrogen is prescribed for a postmenopausal woman with a uterus, progestin should also be initiated to reduce the risk of endometrial cancer. A woman without a uterus does not need progestin. Use of estrogen alone or in combination with a progestin, should be with the lowest effective dose and the shortest duration consistent with treatment goals and risks for the individual woman. Patients should be reevaluated periodically as clinically appropriate (e.g., 3-month to 6-month intervals) to determine whether treatment is still necessary (see BOXED WARNINGS and WARNINGS). For women who have a uterus, adequate diagnostic measures, such as endometrial sampling, when indicated, should be undertaken to rule out malignancy in cases of undiagnosed persistent or recurring abnormal vaginal bleeding.

Patients should be started at the lowest dose. The lowest effective dose of Vivelle-Dot has not been determined for any indication. For treatment of moderate to severe vasomotor symptoms and vulvar and vaginal atrophy associated with the menopause, start therapy with Vivelle-Dot 0.0375 mg/day applied to the skin twice weekly. For the prevention of postmenopausal osteoporosis, start therapy with Vivelle-Dot 0.025 mg/day applied to the skin twice weekly. The dosage may be adjusted as necessary. Reproductive system-associated adverse events were encountered more frequently in the highest dose group (0.1 mg/day) than in other active treatment groups or in placebo-treated patients.

In women not currently taking oral estrogens or in women switching from another estradiol transdermal therapy, treatment with Vivelle-Dot may be initiated at once. In women who are currently taking oral estrogens, treatment with Vivelle-Dot should be initiated 1 week after withdrawal of oral hormone therapy, or sooner if menopausal symptoms reappear in less than 1 week.

Therapeutic Regimen

Vivelle-Dot may be given continuously in patients who do not have an intact uterus. In those patients with an intact uterus, Vivelle-Dot may be given on a cyclic schedule (e.g., three weeks on drug followed by one week off drug).

HOW SUPPLIED

Vivelle-Dot® (estradiol transdermal system), 0.0375 mg/day - each 3.75 cm^2 system contains 0.585 mg of estradiol USP for nominal* delivery of 0.0375 mg of estradiol per day.

Patient Calendar Pack of 8 Systems……………………………………….NDC 54868-4920-0

Vivelle-Dot® (estradiol transdermal system), 0.05 mg/day - each 5.0 cm^2 system contains 0.78 mg of estradiol USP for nominal* delivery of 0.05 mg of estradiol per day.

Patient Calendar Pack of 8 Systems……………………………………….NDC 54868-4242-0

Vivelle-Dot® (estradiol transdermal system), 0.075 mg/day - each 7.5 cm^2 system contains 1.17 mg of estradiol USP for nominal* delivery of 0.075 mg of estradiol per day.

Patient Calendar Pack of 8 Systems……………………………………….NDC 54868-4243-0

Vivelle-Dot® (estradiol transdermal system), 0.1 mg/day - each 10.0 cm^2 system contains 1.56 mg of estradiol USP for nominal* delivery of 0.1 mg of estradiol per day.

Patient Calendar Pack of 8 Systems……………………………………….NDC 54868-4244-0

________________________________________

*See DESCRIPTION.

Store at controlled room temperature at 25ºC (77°F).

Do not store unpouched. Apply immediately upon removal from the protective pouch.

REV: AUGUST 2004 T2004-65

PATIENT INFORMATION

Vivelle-Dot®

(estradiol transdermal system)

Read this PATIENT INFORMATION before you start using Vivelle-Dot® (estradiol transdermal system) and read all the information that you get each time you refill Vivelle-Dot. There may be new information. This information does not take the place of talking to your healthcare provider about your medical condition or your treatment.

The Vivelle-Dot® (estradiol transdermal system) patch that your healthcare provider has prescribed for you releases small amounts of an estrogen hormone through the skin.

This leaflet describes the risks and benefits of treatment with Vivelle-Dot. Vivelle-Dot is not for everyone. Talk to your healthcare provider if you have any questions or concerns about this medication.

WHAT IS THE MOST IMPORTANT INFORMATION I SHOULD KNOW ABOUT VIVELLE-DOT (AN ESTROGEN HORMONE)?

- Estrogens increase the chances of getting cancer of the uterus.

Report any unusual vaginal bleeding right away while you are taking estrogens. Vaginal bleeding after menopause may be a warning sign of cancer of the uterus (womb). Your healthcare provider should check any unusual vaginal bleeding to find out the cause.

- Do not use estrogens with or without progestins to prevent heart disease, heart attacks, or strokes.

Using estrogens with or without progestins may increase your chances of getting heart attacks, strokes, breast cancer, and blood clots. Using estrogens may increase your risk of dementia. You and your healthcare provider should talk regularly about whether you still need treatment with Vivelle-Dot.

What is Vivelle-Dot®?

Vivelle-Dot is a patch that contains the estrogen hormone, estradiol. When applied to the skin as directed below, Vivelle-Dot releases estrogen through the skin into the bloodstream.

What is Vivelle-Dot used for?

Vivelle-Dot is used after menopause to:

● | reduce moderate to severe hot flashes.

Estrogens are hormones made by a woman’s ovaries. The ovaries normally stop making estrogens when a woman is between 45 and 55 years old. This drop in body estrogen levels causes the “change of life” or menopause (the end of monthly menstrual periods). Sometimes, both ovaries are removed during an operation before natural menopause takes place. The sudden drop in estrogen levels causes “surgical menopause.”

When the estrogen levels begin dropping, some women develop very uncomfortable symptoms, such as feelings of warmth in the face, neck, and chest or sudden strong feelings of heat and sweating (“hot flashes” or “hot flushes”). In some women, the symptoms are mild and they will not need estrogens. In other women, symptoms can be more severe. You and your healthcare provider should talk regularly about whether you still need treatment with Vivelle-Dot.

● | treat moderate to severe dryness, itching and burning in or around the vagina.

You and your healthcare provider should talk regularly about whether you still need treatment with Vivelle-Dot to control these problems. If you use Vivelle-Dot only to treat your dryness, itching, and burning in and around your vagina, talk with your healthcare provider about whether a topical vaginal product would be better for you.

● | treat certain conditions in which a young woman’s ovaries do not produce enough estrogens naturally.
● | help reduce your chances of getting osteoporosis (thin weak bones).

Osteoporosis from menopause is a thinning of the bones that makes them weaker and easier to break. If you use Vivelle-Dot only to prevent osteoporosis from menopause, talk with your healthcare provider about whether a different treatment or medicine without estrogens might be better for you. You and your healthcare provider should talk regularly about whether you should continue with Vivelle-Dot.

Weight-bearing exercise, like walking or running, and taking calcium and vitamin D supplements may also lower your chances of getting postmenopausal osteoporosis. It is important to talk about exercise and supplements with your healthcare provider before starting them.

Who should not take Vivelle-Dot?

Do not start taking Vivelle-Dot if you:

● | have unusual vaginal bleeding.
● | currently have or have had certain cancers.
 | Estrogens may increase the chances of getting certain types of cancers, including cancer of the breast or uterus. If you have or have had cancer, talk with your healthcare provider about whether you should take Vivelle-Dot.
● | had a stroke or heart attack in the recent past (for example in the past year).
● | currently have or have had blood clots.
● | currently have or have had liver problems.
● | are allergic to Vivelle-Dot or any of its ingredients.
 | See the end of this leaflet for a list of ingredients in Vivelle-Dot.
● | think you may be, or know that you are, pregnant.

Tell your healthcare provider:

● | if you are breast-feeding. The hormone in Vivelle-Dot can pass into your milk.
● | about all of your medical problems. Your healthcare provider may need to check you more carefully if you have certain conditions such as asthma (wheezing), epilepsy (seizures), migraine, endometriosis, lupus, or problems with your heart, liver, thyroid, kidneys, or have high calcium levels in your blood.
● | about all the medicines you take, including prescription and nonprescription medicines, vitamins, and herbal supplements. Some medicines may affect how Vivelle-Dot works. Vivelle-Dot may also affect how other medicines work.
● | if you are going to have surgery or will be on bed rest. You may need to stop taking estrogens.

How should I take Vivelle-Dot?

1. Start at the lowest dose and talk to your healthcare provider about how well that dose is working for you.
2. Estrogens should be used at the lowest dose possible for your treatment, only as long as needed. The lowest effective dose of Vivelle-Dot has not been determined for any indication. You and your healthcare provider should talk regularly (for example, every 3 to 6 months) about the dose you are taking and whether you still need treatment with Vivelle-Dot.

Application Instructions for Vivelle-Dot (estradiol transdermal system)

1. Determine Your Schedule for Your Twice-a-Week Application

- Decide upon which two days you will change your patch.
- Your Vivelle-Dot® (estradiol transdermal system) individual carton contains a calendar card printed on its inner flap. Mark the two-day schedule you plan to follow on your carton’s inner flap.
- BE CONSISTENT.
- If you forget to change your patch on the correct date, apply a new one as soon as you remember.
- No matter what day this happens, stick to the schedule you have marked on the inner flap of your carton (your calendar card).

2. Where to Apply Vivelle-Dot®

- Apply patch to lower abdomen, below the waistline. Avoid the waistline, since clothing may cause the patch to rub off.
- DO NOT APPLY PATCH TO BREASTS.
- When changing your patch, based on your twice-a-week schedule, apply your new patch to a different site. Do not apply a new patch to that same area for at least one week.

3. Before You Apply Vivelle-Dot®

- Make sure your skin is:
- Clean (freshly washed), dry and cool.
- Free of any powder, oil, moisturizer or lotion.
- Free of cuts and/or irritations (rashes or other skin problems).

4. How to Apply Vivelle-Dot®

- Each patch is individually sealed in a protective pouch.
- Tear open the pouch at the tear notch (do not use scissors).
- Remove the patch.

- Apply the patch immediately after removing from pouch.
- Holding the patch with the rigid protective liner facing you, remove half of the liner, which covers the sticky surface of the patch.

- AVOID TOUCHING THE STICKY SIDE OF THE PATCH WITH YOUR FINGERS.
- Using the other half of the rigid protective liner as a handle, apply the sticky side of the patch to the selected area of the abdomen.

- Press the sticky side of the patch firmly into place.
- Smooth it down.
- While still holding the sticky side down, fold back the other half of the patch.

- Grasp an edge of the remaining protective liner and gently pull it off.
- AVOID TOUCHING THE STICKY SIDE OF THE PATCH WITH YOUR FINGERS.

- Press the entire patch firmly into place with the palm of your hand.
- Continue to apply pressure, with the palm of your hand over the patch, for approximately 10 seconds.

- Make sure that the patch is properly adhered to your skin.
- Go over the edges with your finger to ensure good contact around the patch.

PLEASE NOTE:

● | Contact with water while bathing, swimming or showering will not affect the patch.
● | In the event that a patch should fall off, AVOID TOUCHING THE STICKY SIDE WITH YOUR FINGERS. Put the same patch back on a different site, making sure to press the patch firmly into place for at least 10 seconds.
● | Continue to follow your original twice-a-week schedule you have marked on the inner flap of your individual carton (your calendar card).
● | If necessary, if the same patch cannot be reapplied, apply a new patch at another location but continue to follow your original schedule.

5. How to Change and Discard Vivelle-Dot®

● | When changing the patch, peel off the used patch slowly.
● | Fold the used patch in half (sticky sides together) and discard appropriately, in the trash.
● | PLEASE KEEP OUT OF THE REACH OF CHILDREN.
● | If any adhesive residue remains on your skin after removing the patch, allow the area to dry for 15 minutes. Then, gently rub the area with oil or lotion to remove the adhesive from your skin.
● | Keep in mind, the new patch must be applied to a different area of your abdomen. This area must be clean, dry, cool and free of powder, oil or lotion.

What are the possible side effects of estrogens?

Less common but serious side effects include:

—— | Breast cancer
—— | Cancer of the uterus
—— | Stroke
—— | Heart attack
—— | Blood clots
—— | Dementia
—— | Gallbladder disease
—— | Ovarian cancer

These are some of the warning signs of serious side effects:

—— | Breast lumps
—— | Unusual vaginal bleeding
—— | Dizziness and faintness
—— | Changes in speech
—— | Severe headaches
—— | Chest pain
—— | Shortness of breath
—— | Pains in your legs
—— | Changes in vision
—— | Vomiting

Call your healthcare provider right away if you get any of these warning signs, or any other unusual symptom that concerns you.

Common side effects include:

—— | Headache
—— | Breast pain
—— | Irregular vaginal bleeding or spotting
—— | Stomach/abdominal cramps, bloating
—— | Nausea and vomiting
—— | Hair loss

Other side effects include:

—— | High blood pressure
—— | Liver problems
—— | High blood sugar
—— | Fluid retention
—— | Enlargement of benign tumors of the uterus (“fibroids”)
—— | Vaginal yeast infection

Other side effects of Vivelle-Dot may be possible. If you have questions, talk to your healthcare provider or pharmacist.

What can I do to lower my chances of a serious side effect with Vivelle-Dot?

● | Talk with your healthcare provider regularly about whether you should continue taking Vivelle-Dot.
● | If you have a uterus, talk to your healthcare provider about whether the addition of a progestin is right for you.
● | See your healthcare provider right away if you get vaginal bleeding while taking Vivelle-Dot.
● | Have a breast exam and mammogram (breast X-ray) every year unless your healthcare provider tells you something else. If members of your family have had breast cancer or if you have ever had breast lumps or an abnormal mammogram, you may need to have breast exams more often.
● | If you have high blood pressure, high cholesterol (fat in the blood), diabetes, are overweight, or if you use tobacco, you may have higher chances of getting heart disease. Ask your healthcare provider for ways to lower your chances of getting heart disease.

General information about safe and effective use of Vivelle-Dot

Medicines are sometimes prescribed for conditions that are not mentioned in patient information leaflets. Do not take Vivelle-Dot for conditions for which it was not prescribed. Do not give Vivelle-Dot to other people, even if they have the same symptoms you have. It may harm them. Keep Vivelle-Dot out of the reach of children.

This leaflet provides a summary of the most important information about Vivelle-Dot. If you would like more information, talk with your healthcare provider or pharmacist. You can ask for information about Vivelle-Dot that is written for health professionals. You can get more information by calling the toll-free number [(888-NOW-NOVA) (888-669-6682)].

What are the ingredients in Vivelle-Dot?

Vivelle-Dot is comprised of three layers. Proceeding from the visible surface toward the surface attached to the skin, these layers are (1) a translucent polyolefin film (2) an adhesive formulation containing estradiol, acrylic adhesive, silicone adhesive, oleyl alcohol, NF, povidone, USP and dipropylene glycol, and (3) a polyester release liner which is attached to the adhesive surface and must be removed before the system can be used.

The active component of the system is estradiol. The remaining components of the system are pharmacologically inactive.

Other Information

Do not store above 25ºC (77ºF). Do not store outside of their pouches. Apply immediately upon removal from the protective pouch.

T2004-66

REV: AUGUST 2004 T2004-65/T2004-66

100922-6

Manufactured by:

Noven Pharmaceuticals Inc.

Miami, FL 33186

Distributed by:

Novartis Pharmaceuticals Corporation

East Hanover, NJ 07936

© Novartis

Additional barcode labeling by:
Physicians Total Care, Inc.
Tulsa, Oklahoma 74146

PRINCIPAL DISPLAY PANEL

Package Label – 0.0375 mg

Rx Only NDC 54868-4920-0

Vivelle Dot® (estradiol transdermal system)

Delivers 0.0375 mg/day

Includes 8 Systems

For additional information go to: www.vivelledot.com

PRINCIPAL DISPLAY PANEL

Package Label – 0.05 mg

Rx Only NDC 54868-4242-0

Vivelle Dot® (estradiol transdermal system)

Delivers 0.05 mg/day

Includes 8 Systems

For additional information go to: www.vivelledot.com

PRINCIPAL DISPLAY PANEL

Package Label – 0.075 mg

Rx Only NDC 54868-4243-0

Vivelle Dot® (estradiol transdermal system)

Delivers 0.075 mg/day

Includes 8 Systems

For additional information go to: www.vivelledot.com

PRINCIPAL DISPLAY PANEL

Package Label – 0.1 mg

Rx Only NDC 54868-4244-0

Vivelle Dot® (estradiol transdermal system)

Delivers 0.1 mg/day

Includes 8 Systems

For additional information go to: www.vivelledot.com